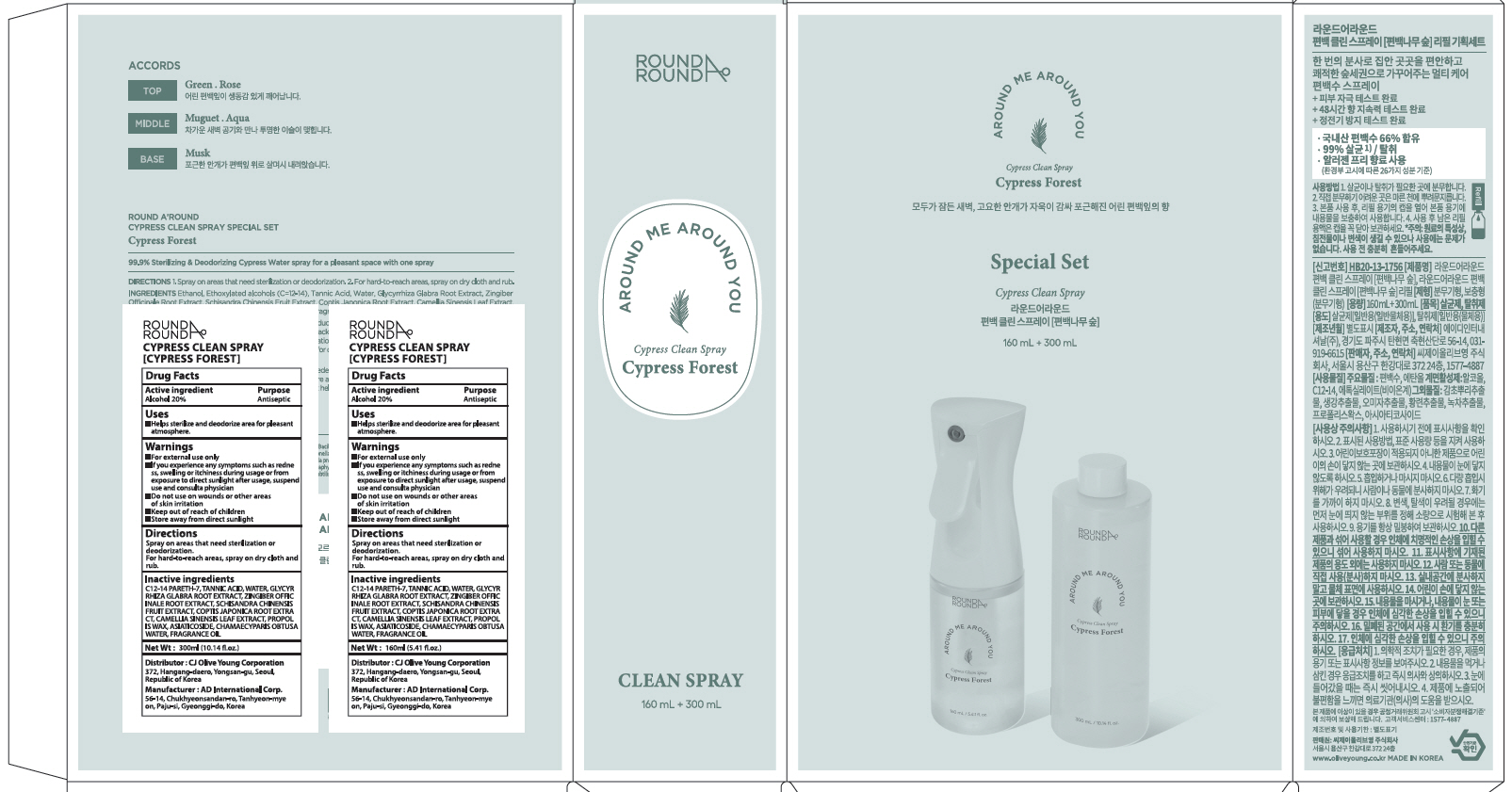 DRUG LABEL: ROUND AROUND CYPRESS CLEAN SP RAY CYPRESS FOREST
NDC: 81540-070 | Form: LIQUID
Manufacturer: CJ Olive Young Corporation
Category: otc | Type: HUMAN OTC DRUG LABEL
Date: 20220810

ACTIVE INGREDIENTS: Alcohol 20 mL/100 mL
INACTIVE INGREDIENTS: C12-14 PARETH-7; TANNIC ACID; WATER

ACTIVE INGREDIENT

Alcohol 20%

INACTIVE INGREDIENTS

C12-14 PARETH-7, TANNIC ACID, WATER, GLYCYRRHIZA GLABRA ROOT EXTRACT, ZINGIBER OFFICINALE ROOT EXTRACT, SCHISANDRA CHINENSIS FRUIT EXTRACT, COPTIS JAPONICA ROOT EXTRACT, CAMELLIA SINENSIS LEAF EXTRACT, PROPOLIS WAX, ASIATICOSIDE, CHAMAECYPARIS OBTUSA WATER, FRAGRANCE OIL

PURPOSE

Antiseptic

WARNINGS

■ For external use only
■ If you experience any symptoms such as redness, swelling or itchiness during usage or from exposure to direct sunlight after usage, suspend use and consult a physician
■ Do not use on wounds or other areas of skin irritation
■ Keep out of reach of children
■ Store away from direct sunlight

KEEP OUT OF REACH OF CHILDREN

Uses

■ Helps sterilize and deodorize area for pleasant atmosphere.

Directions

Spray on areas that need sterilization or deodorization. For hard-to-reach areas, spray on dry cloth and rub.